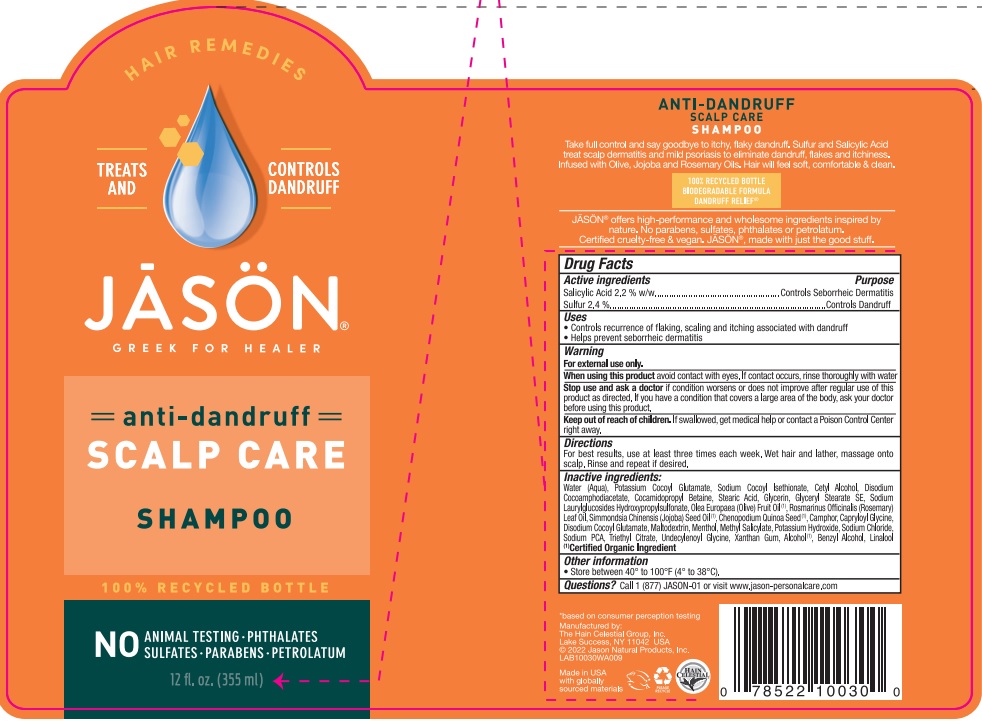 DRUG LABEL: J1003005 Jason Dandruff Relief
NDC: 61995-0030 | Form: SHAMPOO
Manufacturer: The Hain Celestial Group, Inc.
Category: otc | Type: HUMAN OTC DRUG LABEL
Date: 20240731

ACTIVE INGREDIENTS: SULFUR 2.4 g/100 g; SALICYLIC ACID 2.2 g/100 g
INACTIVE INGREDIENTS: SODIUM LAURYLGLUCOSIDES HYDROXYPROPYLSULFONATE; GLYCERYL STEARATE SE; CHENOPODIUM QUINOA SEED; WATER; SODIUM COCOYL ISETHIONATE; DISODIUM COCOAMPHODIACETATE; STEARIC ACID; GLYCERIN; CETYL ALCOHOL; COCAMIDOPROPYL BETAINE; MALTODEXTRIN; OLIVE OIL; ROSEMARY OIL; JOJOBA OIL; CAMPHOR (NATURAL); MENTHOL; METHYL SALICYLATE; POTASSIUM HYDROXIDE; SODIUM PYRROLIDONE CARBOXYLATE; XANTHAN GUM; BENZYL ALCOHOL; CAPRYLOYL GLYCINE; UNDECYLENOYL GLYCINE; LINALOOL, (+/-)-; ALCOHOL; POTASSIUM COCOYL GLUTAMATE; TRIETHYL CITRATE; SODIUM CHLORIDE; DISODIUM COCOYL GLUTAMATE

J10030 Jason Dandruff Shampoo
Formula PF161761-02

ACTIVE INGREDIENT

Sulfur 2.4%

Salicylic Acid 2.2%

PURPOSE

Sulfur Controls Dandruff

Salicylic Acid Controls Seborrheic Dermatitis

INDICATIONS AND USAGE

- Controls recurrence of flaking, scaling and itching associated with dandruff
- Helps prevent seborrheic dermatitis

WARNINGS

For external use only . Avoid contact with eyes.Rinse eyes throughly with water in case contact occurs.Discontinue use and consult your physician if irritation develops.

Keep out of reach of children. If swallowed get medical help or contact Poison Center right away.

DOSAGE AND ADMINISTRATION

For best results, use at least three times each week. Wet hair and lather,massage into scalp. Rinse and repeat if desired.

INACTIVE INGREDIENT

Water (Aqua), Potassium Cocoyl Glutamate, Sodium Cocoyl Isethionate, Cetyl Alcohol, Disodium Cocoamphodiacetate, Cocamidopropyl Betaine, Stearic Acid, Glycerin, Glyceryl Stearate SE, Sodium Laurylglucosides Hydroxypropylsulfonate, Olea Europaea (Olive) Fruit Oil (1), Rosmarinus Officinalis (Rosemary) Leaf Oil, Simmondsia Chinensis (Jojoba) Seed Oil (1), Chenopodium Quinoa Seed (1), Camphor, Capryloyl Glycine, Disodium Cocoyl Glutamate, Maltodextrin, Menthol, Methyl Salicylate, Potassium Hydroxide, Sodium Chloride, Sodium PCA, Triethyl Citrate, Undecylenoyl Glycine, Xanthan Gum, Alcohol (1), Benzyl Alcohol, Linalool

(1) Certified Organic Ingredients